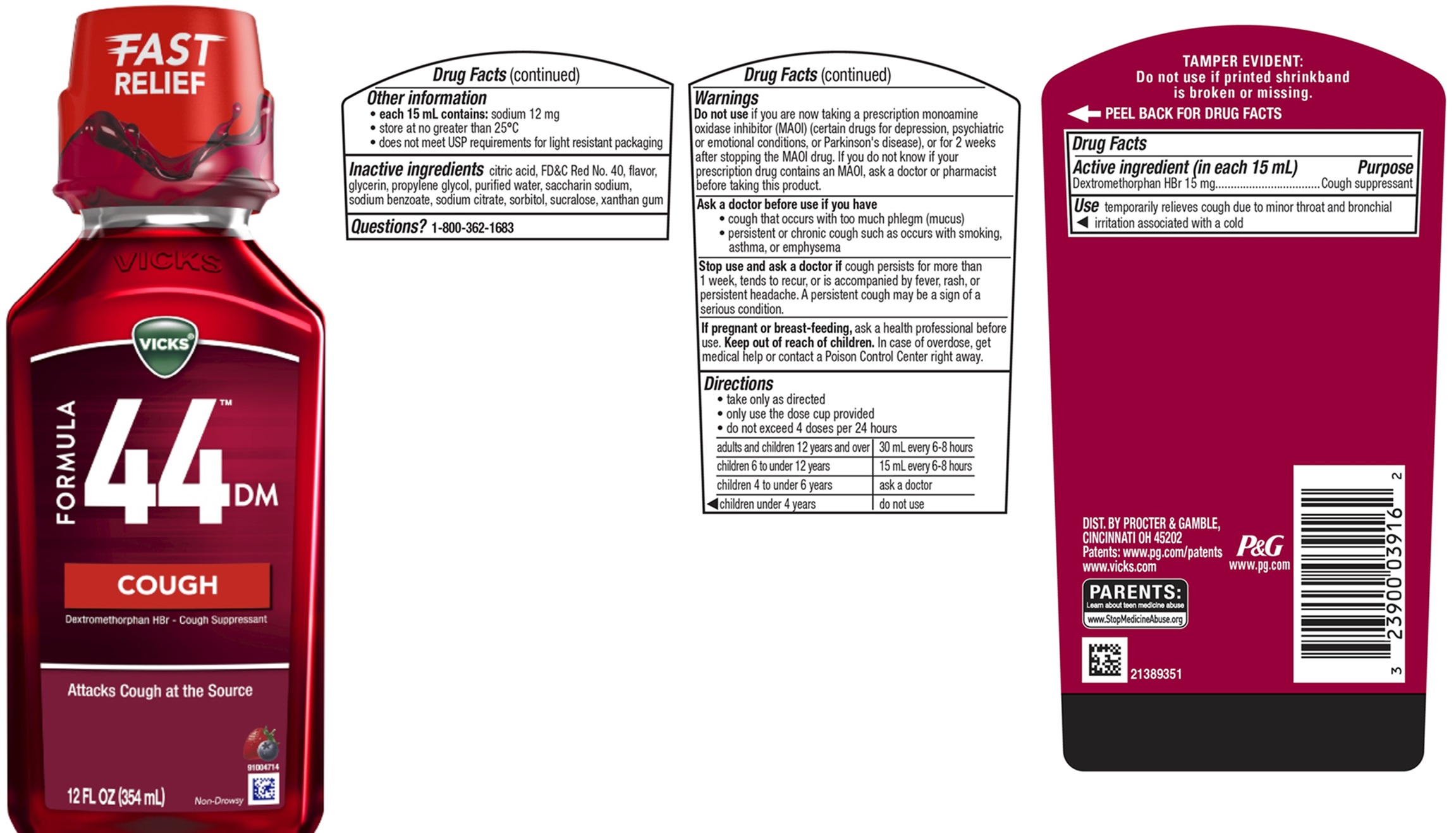 DRUG LABEL: VICKS FORMULA 44DM
NDC: 69423-809 | Form: LIQUID
Manufacturer: The Procter & Gamble Manufacturing Company
Category: otc | Type: HUMAN OTC DRUG LABEL
Date: 20251202

ACTIVE INGREDIENTS: DEXTROMETHORPHAN HYDROBROMIDE 15 mg/15 mL
INACTIVE INGREDIENTS: CITRIC ACID MONOHYDRATE; FD&C RED NO. 40; SODIUM BENZOATE; PROPYLENE GLYCOL; WATER; SACCHARIN SODIUM; SODIUM CITRATE; SORBITOL; GLYCERIN; SUCRALOSE; XANTHAN GUM

VICKS®FORMULA 44™DM COUGH Liquid

Drug Facts

Active ingredient (in each 15 mL)

Dextromethorphan HBr 15 mg

Purpose

Cough suppressant

Use

temporarily relieves cough due to minor throat and bronchial irritation associated with a cold

Warnings

Do not useif you are now taking a prescription monoamine oxidase inhibitor (MAOI) (certain drugs for depression, psychiatric or emotional conditions, or Parkinson's disease), or for 2 weeks after stopping the MAOI drug. If you do not know if your prescription drug contains an MAOI, ask a doctor or pharmacist before taking this product.

Ask a doctor before use if you have

- cough that occurs with too much phlegm (mucus)
- persistent or chronic cough such as occurs with smoking, asthma, or emphysema

Stop use and ask a doctor if

cough persists for more than 1 week, tends to recur, or is accompanied by fever, rash, or persistent headache. A persistent cough may be a sign of a serious condition.

If pregnant or breast-feeding,

ask a health professional before use.

Keep out of reach of children.

OVERDOSAGE

In case of overdose, get medical help or contact a Poison Control Center right away.

Directions

- take only as directed
- only use the dose cup provided
- do not exceed 4 doses per 24 hours

adults and children 12 years and over | 30 mL every 6-8 hours
children 6 to under 12 years | 15 mL every 6-8 hours
children 4 to under 6 years | ask a doctor
children under 4 years | do not use

Other information

• each 15 mL contains:sodium 12 mg
• store at no greater than 25°C
• does not meet USP requirements for light resistant packaging

Inactive ingredients

citric acid, FD&C Red No. 40, flavor, glycerin, propylene glycol, purified water, saccharin sodium, sodium benzoate, sodium citrate, sorbitol, sucralose, xanthan gum

Questions?

1-800-362-1683

TAMPER EVIDENT: Do not use if printed shrinkband is broken or missing.

DIST. BY PROCTER & GAMBLE,
CINCINNATI OH 45202

PRINCIPAL DISPLAY PANEL - 354 ml Bottle Label

VICKS®

FORMULA

44™ DM

COUGH

Dextromethorphan HBr -cough suppressant

ATTACKS COUGH AT THE SOURCE

Non-Drowsy

12 FL OZ (354 ml)